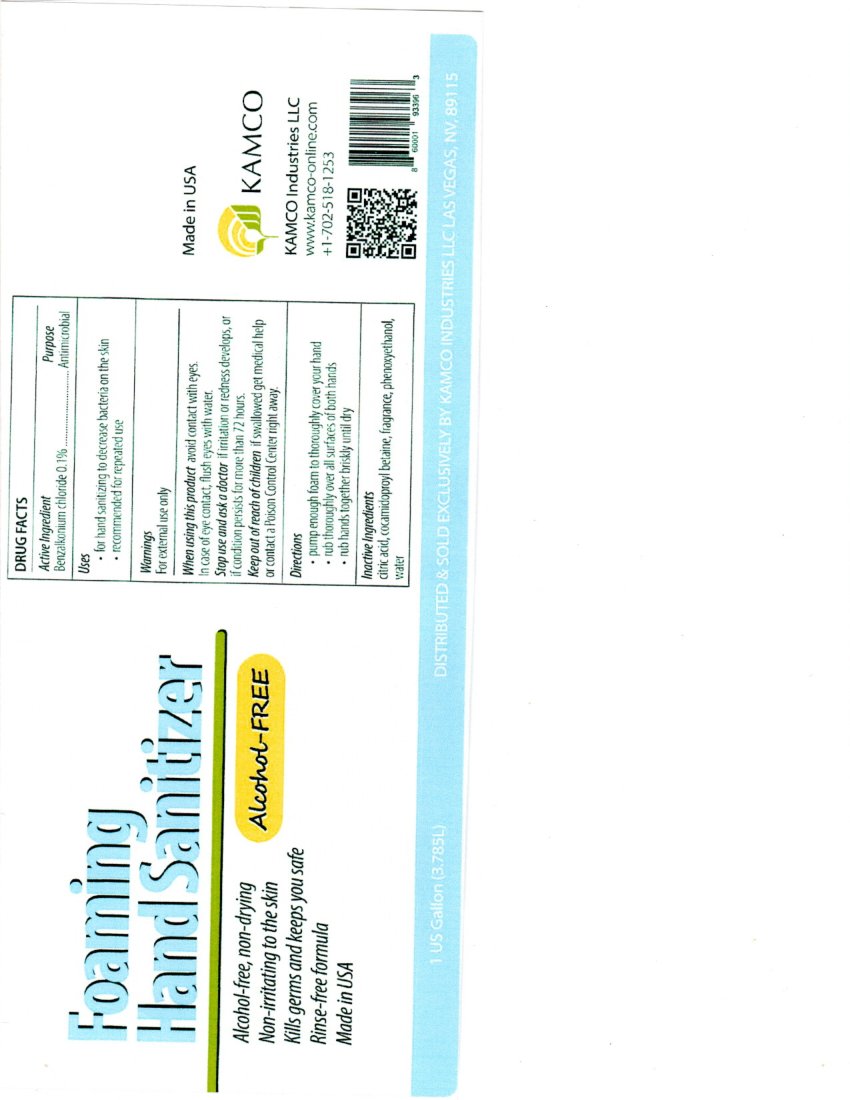 DRUG LABEL: Foaming Hand Sanitizer
NDC: 23261-100 | Form: AEROSOL, FOAM
Manufacturer: Sanitor Corporation
Category: otc | Type: HUMAN OTC DRUG LABEL
Date: 20211222

ACTIVE INGREDIENTS: BENZALKONIUM CHLORIDE 0.1 g/100 g
INACTIVE INGREDIENTS: COCAMIDOPROPYL BETAINE; PHENOXYETHANOL; FRAGRANCE ORANGE ORC2000765; WATER

Foaming Hand Sanitizer

Active Ingredient:

Benzalkonium Chloride 0.1%

Purpose

Antimicrobial

Uses

for hand sanitizing to decrease bacteria on the skin

recommended for repeated use

Warnings

For external use only

When using this product

avoid contact with eyes.

In case of contact, flush eyes with water.

Stop use and ask doctor

if irritation or redness develops, or if condition persists for than 72 hours.

Keep out of reach of children

if swallowed get medical help or contact a Poison Control Center right away.

Directions

pump enough foam to thoroughly cover your hand

rub thoroughly over all surfaces of both hands

rub hands together briskly until dry

Inactive Ingredients:

Citric Acid, Cocamidopropyl Betaine, Fragrance, Phenoxyethanol, Water